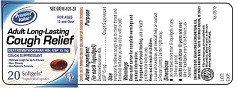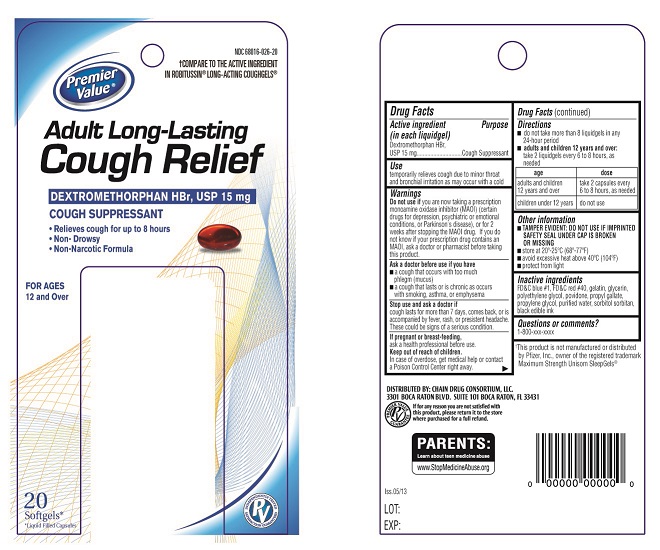 DRUG LABEL: Adult Long Lasting-Cough Relief
NDC: 68016-026 | Form: CAPSULE
Manufacturer: Chain Drug Consortium LLC
Category: otc | Type: Human OTC Drug Label
Date: 20130521

ACTIVE INGREDIENTS: DEXTROMETHORPHAN HYDROBROMIDE 15 mg/1 1
INACTIVE INGREDIENTS: GELATIN; SORBITAN; SORBITOL; FD&C BLUE NO. 1; WATER; POLYETHYLENE GLYCOL 400; POVIDONE K30; GLYCERIN; FD&C RED NO. 40; PROPYLENE GLYCOL

ACTIVE INGREDIENT(S)

Dextromethorphan HBr, USP 15 mg

PURPOSE

Cough Suppressant

USE(S)

Temporarily relieves cough due to minor throat and bronchial irritation as may occur with a cold.

WARNINGS

DO NOT USEYou are now taking a prescription monoamine oxidase inhibitor (MAOI) (certain drugs for depression, psychiatric or emotional conditions, or Parkinson's disease), or for 2 weeks after stopping the MAOI drug. If you do not know if your prescription drug contains an MAOI, ask a doctor or pharmacist before taking this product.

ASK A DOCTOR BEFORE USE IF

- a cough that occurs with too much phlegm (mucus)
- a cough that lasts or is chronic as occurs with smoking, asthma, or emphysema

STOP USE AND ASK DOCTOR IF

Cough lasts for more than 7 days, comes back, or is accompanied by fever, rash, or persistent headache. These could be signs of a serious condition.

PREGNANCY/BREASTFEEDING

Ask a health professional before use.

KEEP OUT OF REACH OF CHILDREN

In case of overdose, get medical help or contact a Poison Control Center right away.

DIRECTIONS

- do not take more than 8 liquidgels in any 24-hour period
- adults and children 12 years and over: take 2 liquidgels every 6 to 8 hours, as needed
- children under 12 years: ask a doctor

STORAGE

- TAMPER EVIDENT: DO NOT USE IF IMPRINTED SAFETY SEAL UNDER CAP IS BROKEN OR MISSING
- store at 20º-25ºC (68º-77ºF)
- avoid excessive heat above 40ºC (104ºF)
- protect from light
- use by expiration date on package

INACTIVE INGREDIENTS

Gelatin, Sorbitol, Sorbitan, FD&C Blue No.1, Water, Polyethylene Glycol 400, Povidone K-30, Glycerine, FD&C Red No. 40, Propylene Glycol.

PRINCIPAL DISPLAY PANEL

CARTON LABEL PDP
NDC # 68016-026-20
Adult Long-Lasting Cough Relief
DEXTROMETHORPHAN HBr, USP 15mg
COUGH SUPPRESSANT
Relieves cough for upto 8 hours
Non-drowsy
Non-Narcotic formula
20 softgels
BOTTLE LABEL PDP
NDC # 68016-026-20
Adult Long-Lasting Cough Relief
DEXTROMETHORPHAN HBr, USP 15mg
COUGH SUPPRESSANT
Relieves cough for about 8 hours
Non-Drowsy
Non-Narcotic Formula
20 Softgels